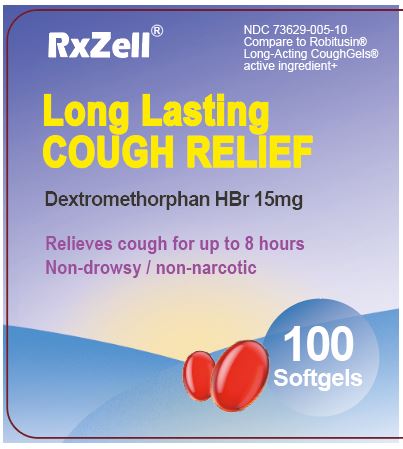 DRUG LABEL: DEXTROMETHORPHAN HBR 15 MG
NDC: 73629-005 | Form: CAPSULE, LIQUID FILLED
Manufacturer: AMZ789 LLC
Category: otc | Type: HUMAN OTC DRUG LABEL
Date: 20250108

ACTIVE INGREDIENTS: DEXTROMETHORPHAN HYDROBROMIDE 15 mg/1 1
INACTIVE INGREDIENTS: WATER; FD&C RED NO. 40; POLYETHYLENE GLYCOL 400; POVIDONE; GELATIN; PROPYLENE GLYCOL; FD&C BLUE NO. 1; GLYCERIN; SORBITOL

DEXTROMETHORPHAN HBR 15 MG

ACTIVE INGREDIENT

Dextromethorphan HBr, USP 15 mg

PURPOSE

Cough suppressant

Use

temporarily relieves cough due to minor throat and bronchial irritation as may occur with a cold

Do not use if you are now taking a prescription monoamine oxidase inhibitor (MAOI) (certain drugs for depression, psychiatric, or emotional conditions, or Parkinson's disease), or for 2 weeks after stopping the MAOI drug. If you do not know if your prescription drug contains an MAOI, ask a doctor or pharmacist before taking this product.

ASK DOCTOR/PHARMACIST

a cough that occurs with too much phlegm (mucus)
a cough that lasts or is chronic as occurs with smoking, asthma, or emphysema

Stop use and ask a doctor if cough lasts for more than 7 days, comes back, or is accompanied by fever, rash, or persistent headache. These could be signs of a serious condition.

PREGNANCY OR BREAST FEEDING

If pregnant or breast-feeding, ask a health professional before use.

Keep out of reach of children. In case of overdose, get medical help or contact a Poison Control Center right away.

DOSAGE AND ADMINISTRATION

do not take more than 8 capsules in any 24-hour period
this adult product is not intended for use in children under 12 years of age

adults and children 12 years of age and over | take 2 capsules every 6 to 8 hours, as needed
children under 12 years of age | do not use

OTHER SAFETY INFORMATION

store at 20-25°C (68-77°F)
avoid excessive heat above 40°C (104°F)
protect from light

INACTIVE INGREDIENT

FD&C blue #1, FD&C Red #40, gelatin, glycerin, polyethylene glycol, povidone, propylene glycol, purified water, sorbitol special, and white edible ink